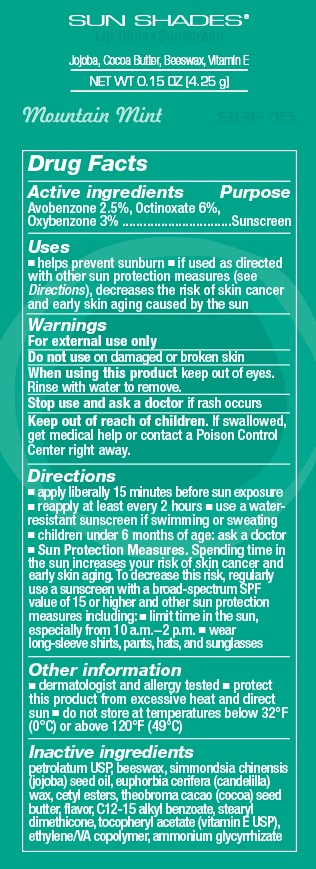 DRUG LABEL: Sun Shades Lip Balm
NDC: 54473-220 | Form: STICK
Manufacturer: Melaleuca Inc.
Category: otc | Type: HUMAN OTC DRUG LABEL
Date: 20251231

ACTIVE INGREDIENTS: AVOBENZONE 0.1175 g/4.25 g; OCTINOXATE 0.282 g/4.25 g; OXYBENZONE 0.141 g/4.25 g
INACTIVE INGREDIENTS: ALKYL (C12-15) BENZOATE; ALPHA-TOCOPHEROL ACETATE; AMMONIUM GLYCYRRHIZATE; CERESIN; CETYL ESTERS WAX; COCOA BUTTER; ETHYLENE-VINYL ACETATE COPOLYMER (40% VINYL ACETATE); JOJOBA OIL; PETROLATUM; YELLOW WAX; CANDELILLA WAX

Sun Shades Lip Balm - Sunscreen
Mountain Mint - Broad-spectrum SPF 15

Active ingredients

Avobenzone 2.5%, Octinoxate 6%, Oxybenzone 3%

Purpose

Sunscreen

Uses

■ helps prevent sunburn ■ if used as directed with other sun protection measures (see Directions), decreases the risk of skin cancer and early skin aging caused by the sun

Warnings

For external use only

Do not use on damaged or broken skin

When using this product keep out of eyes. Rinse with water to remove.

Stop use and ask a dcotor if rash occurs

Keep out of reach of children. If swallowed, get medical help or contact a Poison Control Center right away.

Directions

■ apply liberally 15 minutes before sun exposure

■ reapply at least every 2 hours ■ use a water-resistant sunscreen if swimming or sweating ■ children under 6 months of age: ask a doctor

■ Sun Protection Measures. Spending time in the sun increases your risk of skin cancer and early skin aging. To decrease this risk, regularly use a sunscreen with a broad-spectrum SPF value of 15 or higher and other sun protection measures including: ■ limit time in the sun, especially from 10 a.m.-2 p.m.■ wear long-sleeve shirts, pants, hats, and sunglasses

Other information

■ dermatologist and allergy tested

STORAGE AND HANDLING

■ protect this product from excessive heat and direct sun ■ do not store at temperatures below 32°F (0°C) or above 120°F (49°C)

Inactive Ingredients

petrolatum USP, beeswax, simmondsia chinensis (jojoba) seed oil, euphorbia cerifera (candelilla) wax, cetyl esters, theobroma cacao (cocoa) seed butter, flavor, C12-15 alkyl benzoate, stearyl dimethicone, tocopheryl acetate (vitamin E USP), ethylene/VA copolymer, ammonium glycrrhizate